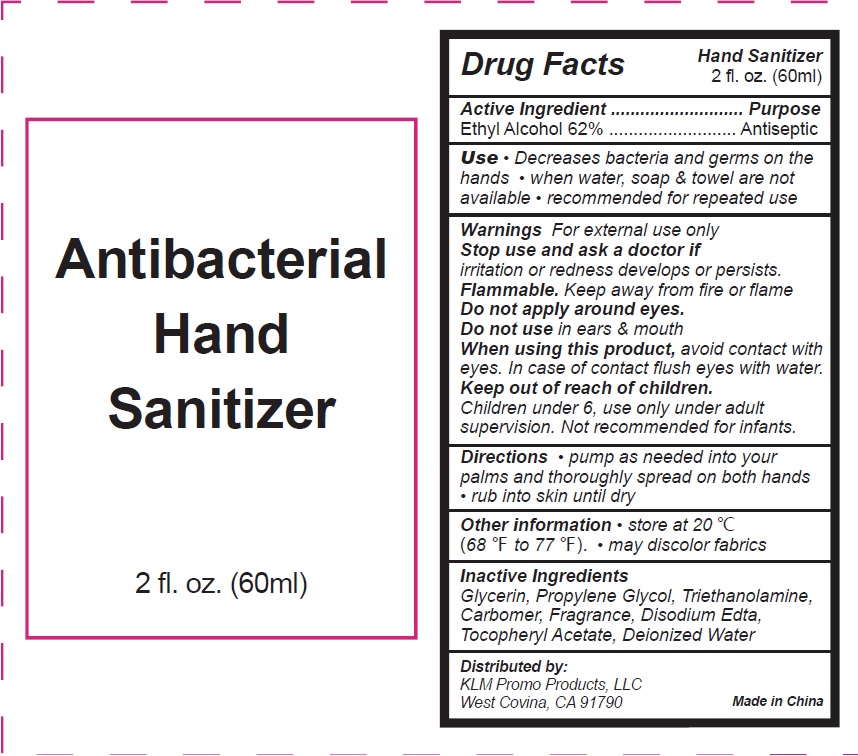 DRUG LABEL: HAND SANITIZER
NDC: 75613-006 | Form: GEL
Manufacturer: Ningbo Lanzi Cosmetic Technology Co., Ltd
Category: otc | Type: HUMAN OTC DRUG LABEL
Date: 20200522

ACTIVE INGREDIENTS: ALCOHOL 62 mL/100 mL
INACTIVE INGREDIENTS: WATER; PROPYLENE GLYCOL; EDETATE DISODIUM; TROLAMINE; .ALPHA.-TOCOPHEROL ACETATE, D-; GLYCERIN

HAND SANITIZER

Active ingredient

Ethyl Alcohol 62%

Purpose

Antiseptic

Use

- Decrease bacteria and germs on the hands.
- When water, soap and towel are not available
- Recommended for repeated use

Warnings

For external use only.

Flammable.Keep away from fire and flame.

Do not apply around eyes.

Do not use in ears and mouth

When using this product

avoid contact with eyes. In case of contact, flush eyes with water.

Avoid contact with broken skin.

Stop use and ask a doctor if

irritation or redness develops or persists.

Keep out of reach of children.

Children under 6, use only under adult supervision. Not recommended for infants.

Directions

- pump as needed into your palms and thoroughly spread on both hands
- rub into skin until dry

Other Information:

- store at 20 ℃ (68 to 77℉)
- may discolor fabrics

Inactive ingredients

Glycerin,Propylene Glycol, Triethanolamine, Carbomer, Fragrance, Disodium Edta, Tocopheryl Acetate, Deionized Water